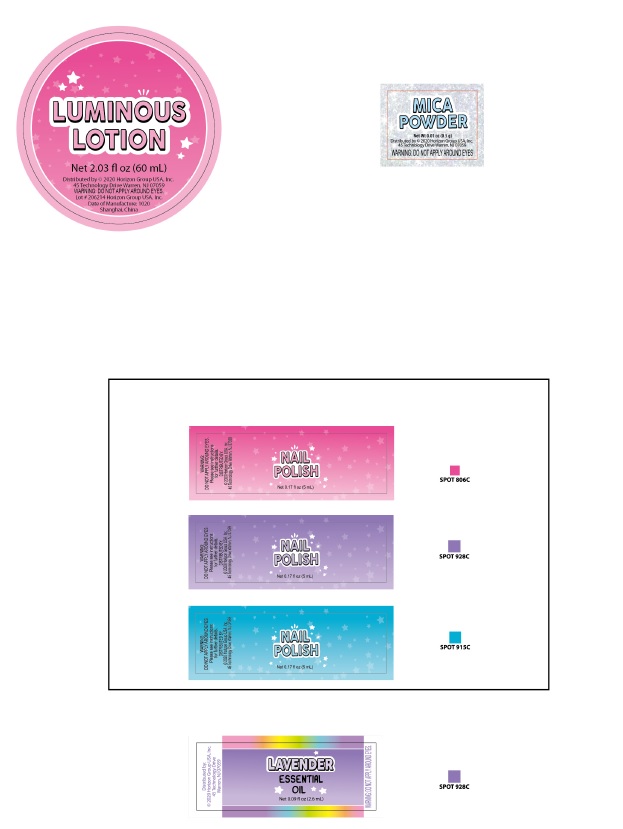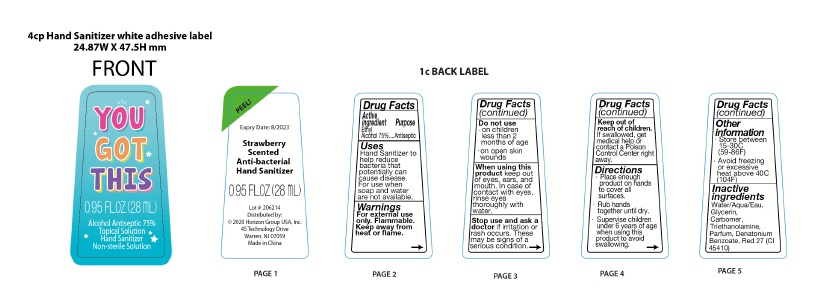 DRUG LABEL: ISM BE-YOU-TIFUL SELF CARE STUDIO
NDC: 80797-001 | Form: GEL
Manufacturer: HORIZON GROUP USA, INC.
Category: otc | Type: HUMAN OTC DRUG LABEL
Date: 20201007

ACTIVE INGREDIENTS: ALCOHOL 75 mL/100 mL
INACTIVE INGREDIENTS: WATER; GLYCERIN; CARBOMER HOMOPOLYMER, UNSPECIFIED TYPE; TROLAMINE; DENATONIUM BENZOATE

ISM BE-YOU-TIFUL SELF CARE STUDIO

Active Ingredients

Ethyl Alcohol

Purpose

Antiseptic

Warnings

- For external use only. Flammable. Keep away from heat or flame.
- Keep out of reach of children. If swallowed, get medical help or contact Poison Control Center right away.
- Do not use in children less than 2 months of age; on open skin wounds
- When using this product keep out of eyes, ears, and mouth.
- In case of contact with eyes, rinse eyes thoroughly with water.
- Stop use and ask a doctor if irritation or rash occurs. These may be signs of a serious condition.

Uses

- Hand Sanitizer to help reduce bacteria that potentially can cause disease.
- For use when soap and water are not available.

Directions

- Place enough product on hands to cover all surfaces. Rub hands together until dry.
- Supervise children under 6 years of age when using this product to avoid swallowing.

Keep out of reach of children.

If swallowed, get medical help or contact Poison Control Center right away.

Other Information

Store between 15-30C (59-86F); Avoid freezing or excessive heat above 40C (104F)

Inactive Ingredient

Water/Aqua/Eau,Glycerin,Carbomer,Triethanolamine,parfum,Denatonium benzoate,Red 27 (CI 45410).